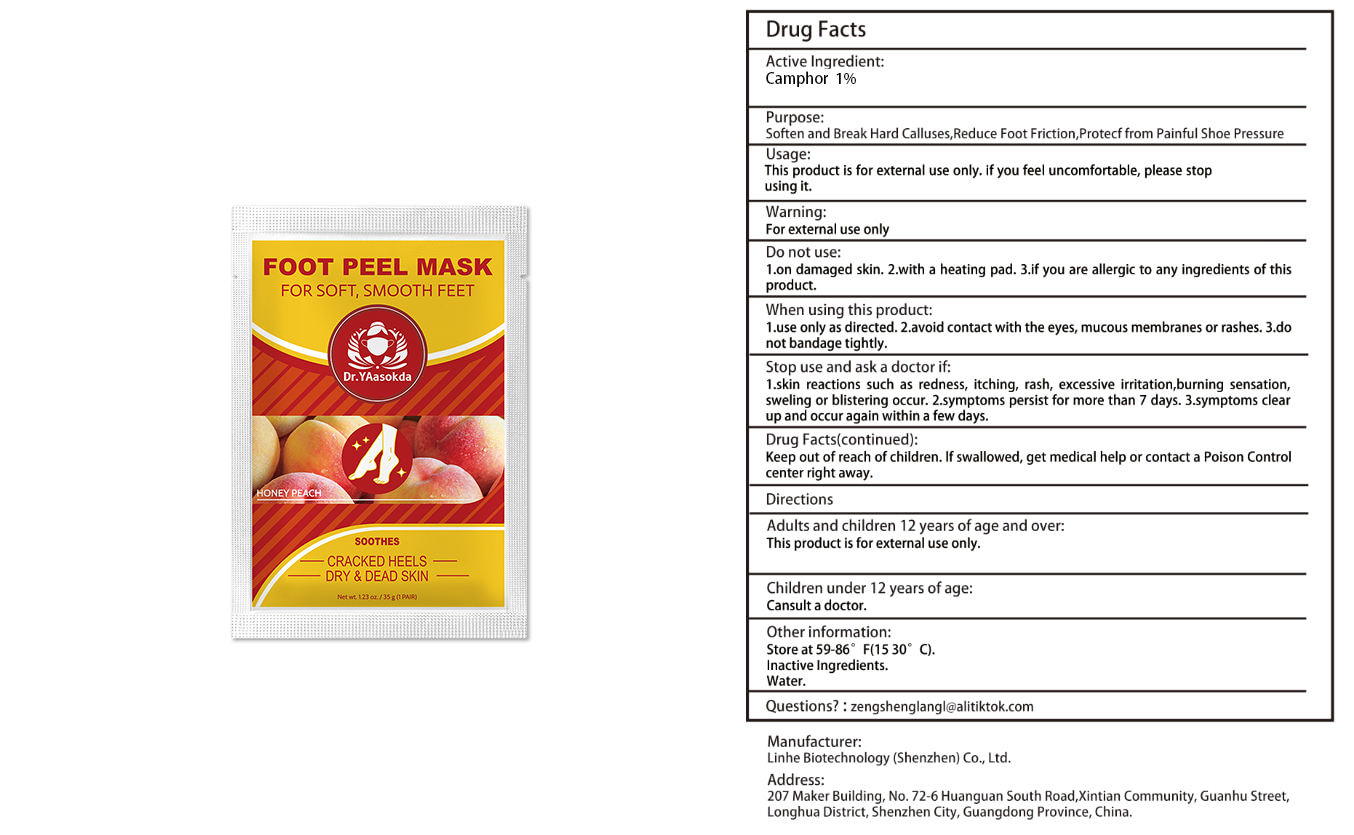 DRUG LABEL: Foot Peel Mask
NDC: 84575-099 | Form: PATCH
Manufacturer: Linhe Biotechnology (Shenzhen) Co., Ltd
Category: otc | Type: HUMAN OTC DRUG LABEL
Date: 20241127

ACTIVE INGREDIENTS: CAMPHOR, (-)- 1.45833333 g/35 g
INACTIVE INGREDIENTS: WATER

CORN CARE PATCHES

ACTIVE INGREDIENT

Camphor 1%

PURPOSE

Soften and Break Hard Calluses,Reduce Foot Friction,Protecf from Painful Shoe Pressure

INDICATIONS AND USAGE

This product is for external use only. if you feel uncomfortable, please stop using it.

WARNINGS

For external use only.
Patients with renal failure and those with low heart rates should not use this product. This product is notintended to diagnose,treat, cure or prevent any disease.

DOSAGE AND ADMINISTRATION

This product is for external use only.

INACTIVE INGREDIENT

WATER

STORAGE AND HANDLING

Store in a cool and dark place away from light

Keep out of reach of children,in case of overdose, get medical help or contact a PoisonControl Center right away.